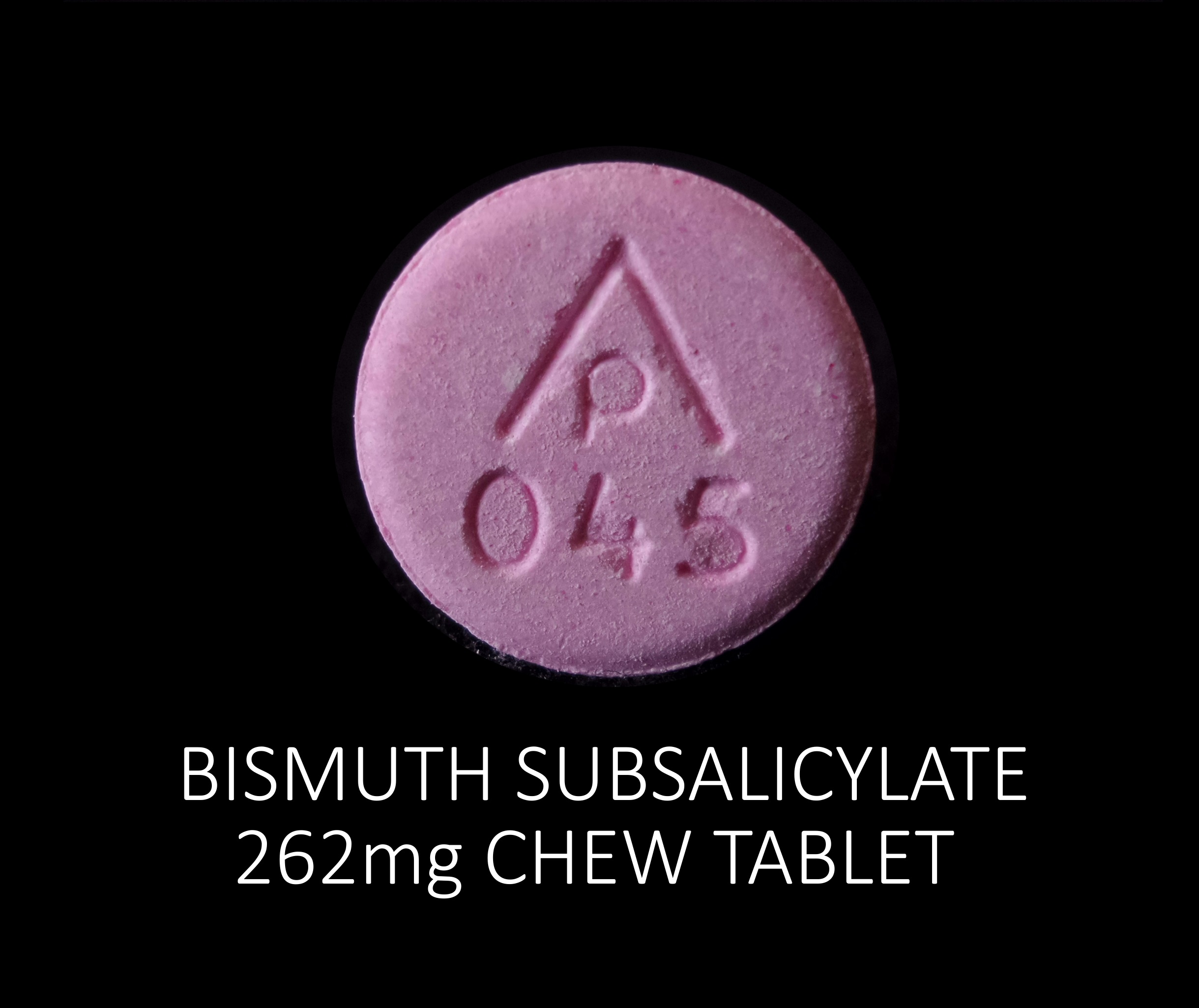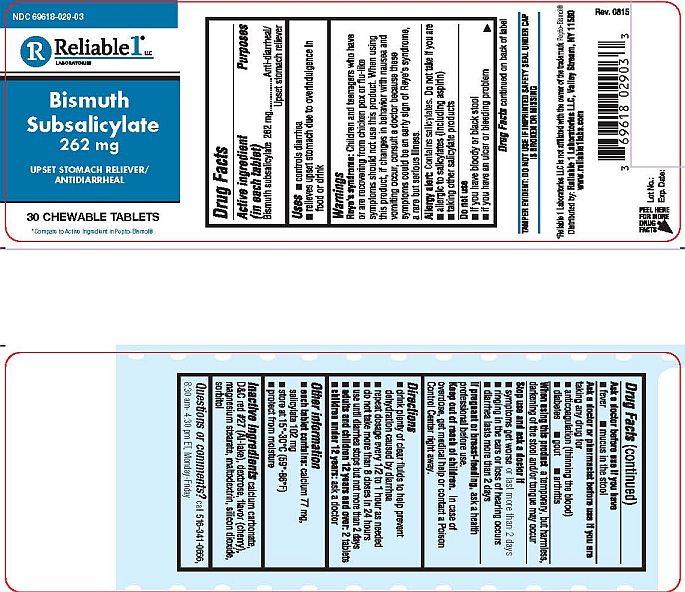 DRUG LABEL: Bismuth Subsalicylate 262 mg
NDC: 69618-029 | Form: TABLET, CHEWABLE
Manufacturer: Reliable 1 Laboratories LLC
Category: otc | Type: HUMAN OTC DRUG LABEL
Date: 20250115

ACTIVE INGREDIENTS: BISMUTH SUBSALICYLATE 262 mg/1 1
INACTIVE INGREDIENTS: CALCIUM CARBONATE; DEXTROSE; CHERRY; MAGNESIUM STEARATE; MALTODEXTRIN; D&C RED NO. 27; SILICON DIOXIDE; SORBITOL

Bismuth Subsalicylate 262 mg

Drug Facts

Active ingredient (in each tablet)

Bismuth subsalicylate 262 mg

Purposes

Anti-diarrheal / Upset stomach reliever

Uses

- controls diarrhea
- relieves upset stomach due to overindulgence in food or drink

Warnings

Reye's syndrome: Children and teenagers who have or are recovering from chicken pox or flu-like symptoms should not use this product. When using this product, if changes in behavior with nausea and vomiting occur, consult a doctor because these symptoms could be an early sign of Reye's syndrome, a rare but serious illness.

Allergy alert: Contains salicylates. Do not take if you are:

- allergic to salicylates (including aspirin)
- taking other salicylate products

Do not use

- if you have bloody or black stool
- if you have an ulcer or bleeding problem

Drug Facts continued on back of label

Ask a doctor before use if you have

- fever
- mucus in the stool

Ask a doctor or pharmacist before use if you are taking any drug for

- anticoagulation (thinning the blood)
- diabetes
- gout
- arthritis

When using this product a temporary, but harmless, darkening of the stool and/or tongue may occur

Stop use and ask a doctor if

- symptoms get worse or last more than 2 days
- ringing in the ears or loss of hearing occurs
- diarrhea lasts more than 2 days

PREGNANCY OR BREAST FEEDING

If pregnant or breast-feeding, ask a health professional before use.

Keep out of reach of children. In case of overdose, get medical help or contact a Poison Control Center right away.

Directions

- drink plenty of clear fluids to help prevent dehydration caused by diarrhea
- repeat dosage every 1/2 to 1 hour as needed
- do not take more than 8 doses in 24 hours
- use until diarrhea stops but not more than 2 days
- adults and children 12 years and over: 2 tablets
- children under 12 years: ask a doctor

Other information

- each tablet contains: calcium 77 mg, salicylate 102 mg
- store at 15°-30°C (59°-86°F)
- protect from moisture

Inactive ingredients

calcium carbonate, D&C red #27 (Al-lake), dextrose, flavor (cherry), magnesium stearate, maltodextrin, silicon dioxide, sorbitol

Questions or comments?

call 516-341-0666, 8:30 am- 4:30 pm ET, Monday-Friday

TAMPER EVIDENT: DO NOT USE IF IMPRINTED SAFETY SEAL UNDER CAP IS BROKEN OR MISSING

*Reliable 1 Laboratories LLC is not affiliated with the owner of the trademark Pepto-Bismol®

Distributed by: Reliable 1 Laboratories LLC, Valley Stream, NY 11580

www.reliable1labs.com

PACKAGE LABEL

NDC 69618-029-03

Bismuth Subsalicylate

262 mg

UPSET STOMACH RELIEVER / ANTIDIARRHEAL

30 CHEWABLE TABLETS

*compare to Active Ingredients in Pepto-Bismol®